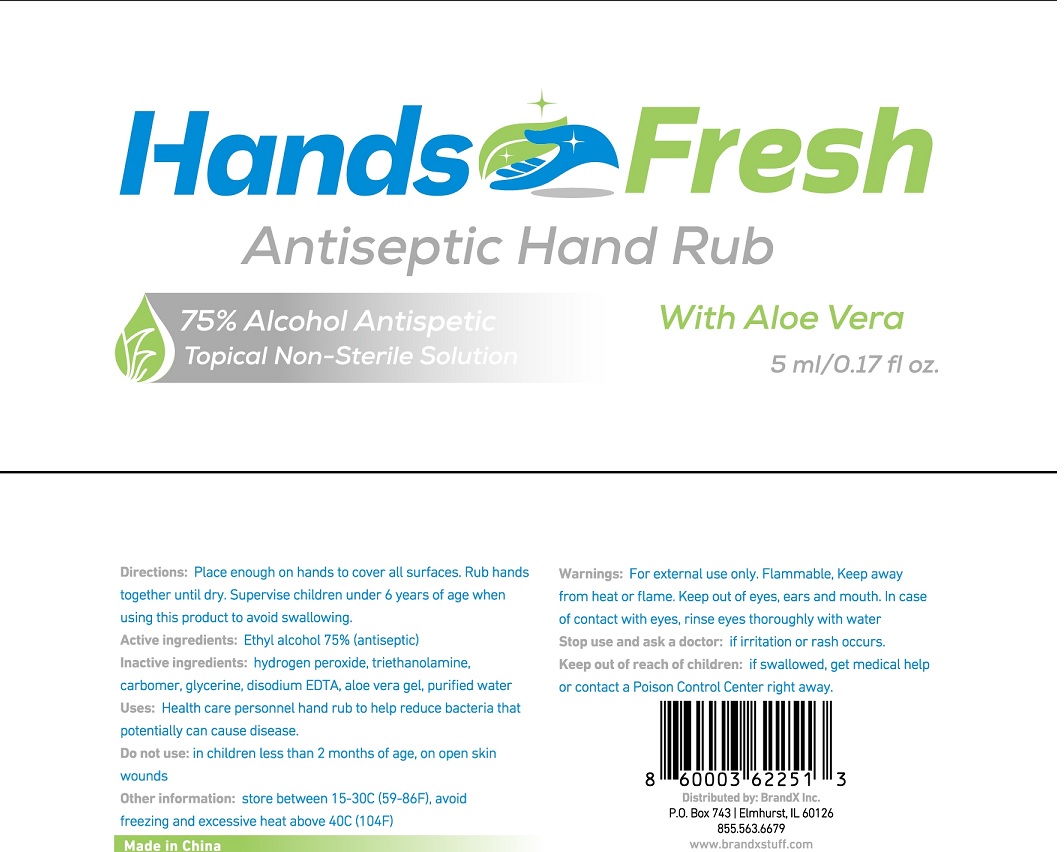 DRUG LABEL: Hands Fresh Antiseptic Hand Rub with aloe vera
NDC: 71734-310 | Form: GEL
Manufacturer: JIANGMEN SHUIZIRUN SANITARY ARTICLES CO., LTD.
Category: otc | Type: HUMAN OTC DRUG LABEL
Date: 20200418

ACTIVE INGREDIENTS: ALCOHOL 75 mL/100 mL
INACTIVE INGREDIENTS: WATER; GLYCERIN; TROLAMINe; CARBOMER 934; EDETATE DISODIUM

Active ingredient

75% Ethyl Alcohol

Purpose

Antiseptic

Use

Health care personnel hand rub to help reduce bacteria that potntially can cause disease.

Warnings

For external use only.

Flammable, Keep way from heat or flame

Keep out of eyes, ears and mouth. In case of contact with eyes, rinse eyes thoroughly with water.

Stop use and ask a doctor: if irritation or rash occurs.

Do not use: in children less than 2 months of age, on open skin wounds.

Keep out of reach of children.

If swallowed, get medical help or contact a Poison Control Center right away.

Directions

- Place enough on hands to cover all surfac. Rub hands together until dry
- Supervise children under 6 years of age when using this products to avoid swallowing.

Inactive ingredients

Hrdrogen peroxide, triethanolamine, Carbomer, Glycerin, Disodium EDTA, aloe vera gel, purified water

Other information

store between 15-30℃ （59-86℉）， avoid freezing and excessive heat above 40℃（104℉）